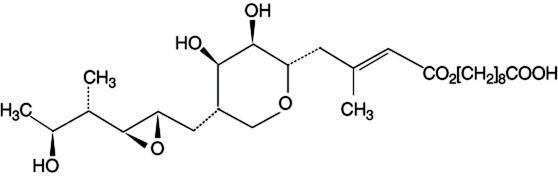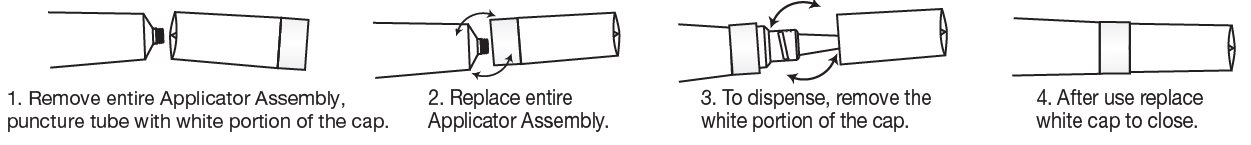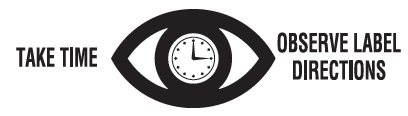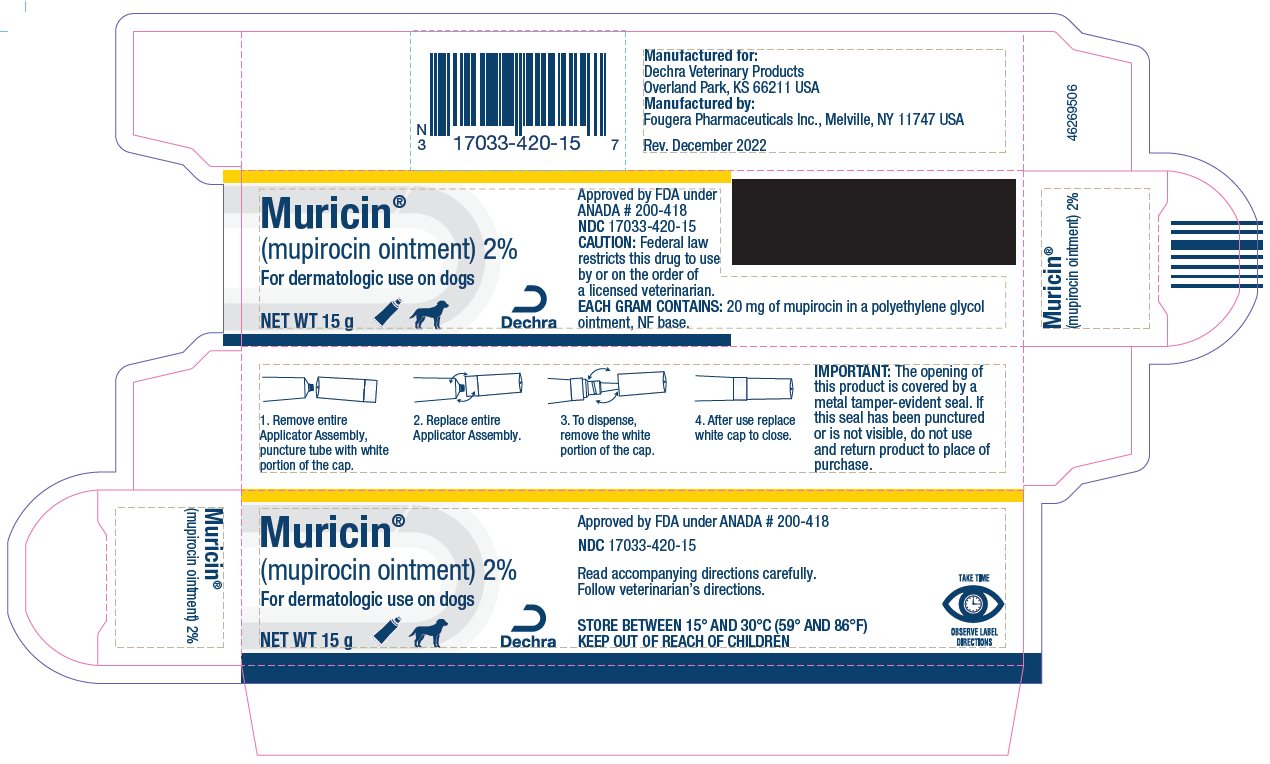 DRUG LABEL: MURICIN
NDC: 17033-420 | Form: OINTMENT
Manufacturer: Dechra Veterinary Products
Category: animal | Type: PRESCRIPTION ANIMAL DRUG LABEL
Date: 20221221

ACTIVE INGREDIENTS: MUPIROCIN 20 mg/1 g
INACTIVE INGREDIENTS: POLYETHYLENE GLYCOL 3350; POLYETHYLENE GLYCOL 400

Muricin®
(mupirocin ointment) 2%

For dermatologic use on dogs.

CAUTION: Federal law restricts this drug to use by or on the order of a licensed veterinarian.

DESCRIPTION:

Each gram of Muricin ointment contains 20 mg of mupirocin in a bland, water-washable ointment base consisting of polyethylene glycol 400 and polyethylene glycol 3350 (polyethylene glycol ointment, NF). Mupirocin is a naturally-occurring, broadspectrum antibiotic. The chemical name is (E)-(2S,3R,4R,5S)-5-[(2S,3S,4S,5S)-2,3-Epoxy-5-hydroxy-4-methylhexyl]tetrahydro-3,4-dihydroxy-β-methyl-2H-pyran-2-crotonic acid, ester with 9-hydroxynonanoic acid. The chemical structure is:

CLINICAL PHARMACOLOGY:

Mupirocin is a chemical entity produced by fermentation of the organism Pseudomonas fluorescens. Mupirocin inhibits bacterial protein synthesis by reversibly and specifically binding to bacterial isoleucyl transfer-RNA synthetase. Due to this mode of action, mupirocin shows no cross resistance with chloramphenicol, erythromycin, gentamicin, lincomycin, neomycin, novobiocin, penicillin, streptomycin, and tetracycline. Mupirocin is an antimicrobial agent that inhibits the growth of Gram-positive and Gram-negative bacteria. Bacteria susceptible to the action of mupirocin in vitro include the aerobic isolates of Staphylococcus aureus (including methicillin-resistant strains and β-lactamase-producing strains), Staphylococcus intermedius, Staphylococcus epidermidis, other coagulase positive or negative Staphylococci, α-hemolytic Streptococci, β group A Streptococci (including S. pyogenes), other β Streptococci (including S. agalactiae), group D Streptococci (including S. faecalis and S. faecium), group Viridans Streptococci, Streptococcus pneumoniae, Corynebacterium hofmanii, Bacillus subtilis, Escherichia coli, Klebsiella pneumoniae, Proteus mirabilis, Proteus vulgaris, Enterobacter cloacae, Enterobacter aerogenes, Citrobacter freundii, Hemophilus influenzae (including β-lactamase-producing strains), Neisseria gonorrheae (including β-lactamase-producing strains), Neisseria meningitidis, Branhamella catarrhalis and Pasteurella multocida, and the anaerobic isolates of Peptostreptococcus anaerobius, Clostridium difficile, and Clostridium sporogenes.

Clinical significance of the in vitro data is unknown except for susceptible strains of Staphylococcus aureus and Staphylococcus intermedius.

INDICATIONS FOR USE:

Muricin ointment is indicated for the topical treatment of canine bacterial infections of the skin, including superficial pyoderma, caused by susceptible strains of Staphylococcus aureus and Staphylococcus intermedius.

CONTRAINDICATIONS:

This drug is contraindicated in animals with a history of sensitivity reactions to any of its components.

WARNINGS:

Because of the potential hazard of nephrotoxicity due to the polyethylene glycol content of the base, care should be exercised when using this product in treating extensive deep lesions where absorption of large quantities of polyethylene glycol is possible.
Safety of use in pregnant or breeding animals has not been determined. Muricin ointment is not for ophthalmic use.

ADVERSE REACTIONS:

No adverse reactions have been reported with this product. If a skin reaction such as irritation should occur, treatment should be discontinued and appropriate therapy instituted.

To report suspected adverse drug events, for technical assistance, or to obtain a copy of the Safety Data Sheet, contact Dechra Veterinary Products at (866) 933-2472.

For additional information about adverse drug experience reporting for animal drugs, contact FDA at 1-888-FDA-VETS or http://www.fda.gov/reportanimalae.

DOSAGE AND ADMINISTRATION:

Prior to treatment, the lesion should be cleansed. Muricin ointment should be applied to the affected area twice a day. Apply a sufficient amount of ointment to completely cover the infected area. Maximum duration of treatment should not exceed 30 days.

HOW SUPPLIED:

Muricin ointment is supplied in 15-gram tubes.

NDC 17033-420-15.

Store between 15° and 30°C (59° and 86°F).

Keep out of reach of children.

IMPORTANT:

The opening of this product is covered by a metal tamper-evident seal.

If this seal has been punctured or is not visible, do not use and return product to place of purchase.

Approved by FDA under ANADA # 200-418

Manufactured for:

Dechra Veterinary Products

Overland Park, KS 66211 USA

Manufactured by:

Fougera Pharmaceuticals Inc.

Melville, NY 11747 USA

46269504

Rev. December 2022

PRINCIPAL DISPLAY PANEL - 15 g Carton

Muricin®
(mupirocin ointment) 2%
For dermatologic use on dogs
NET WT 15 g
NDC 17033-420-15